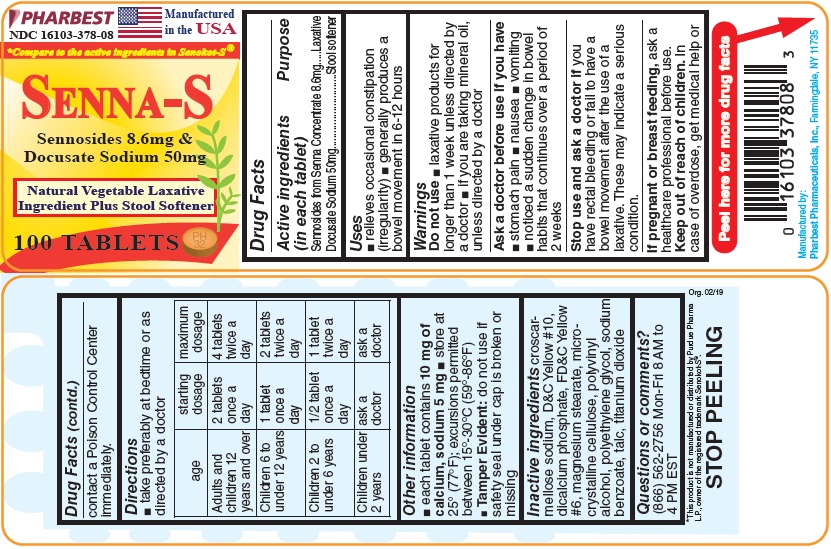 DRUG LABEL: Senna-S
NDC: 16103-378 | Form: TABLET, FILM COATED
Manufacturer: Pharbest Pharmaceuticals, Inc.
Category: otc | Type: HUMAN OTC DRUG LABEL
Date: 20251224

ACTIVE INGREDIENTS: SENNOSIDES 8.6 mg/1 1; DOCUSATE SODIUM 50 mg/1 1
INACTIVE INGREDIENTS: CROSCARMELLOSE SODIUM; D&C YELLOW NO. 10; CALCIUM PHOSPHATE, DIBASIC, DIHYDRATE; FD&C YELLOW NO. 6; MAGNESIUM STEARATE; CELLULOSE, MICROCRYSTALLINE; POLYVINYL ALCOHOL, UNSPECIFIED; POLYETHYLENE GLYCOL, UNSPECIFIED; SODIUM BENZOATE; TALC; TITANIUM DIOXIDE

Drug Facts

Active Ingredients (in each tablet)

Sennosides from Senna Concentrate 8.6mg

Docusate Sodium 50mg

Purpose

Laxative

Stool Softner

Uses

- relieves occasional constipation (irregularity)
- generally produces a bowel movement in 6-12 hours

Warnings

Do not use

- laxative products for longer than 1 week unless directed by a doctor
- if you are taking mineral oil, unless directed by a doctor

Ask a doctor before use if you have

- stomach pain
- nausea
- vomiting
- noticed a sudden change in bowel habits that continues over a period of 2 weeks

Stop use and ask a doctor if

you have rectal bleeding or fail to have a bowel movement after the use of a laxative. These may indicate a serious condition.

If pregnant or breast feeding,

ask a healthcare professional before use.

Keep out of reach of children.

In case of overdose, get medical help or contact a Poison Control Center immediately.

Directions

- take preferably at bedtime or as directed by a doctor

age | starting dosage | maximum dosage
Adults and children 12 years and over | 2 tablets once a day | 4 tablets twice a day
Children 6 to under 12 years | 1 tablet once a day | 2 tablets twice a day
Children 2 to under 6 years | 1/2 tablet once a day | 1 tablet twice a day
Children under 2 years | ask a doctor | ask a doctor

Other information

- each tablet contains 10 mg of calcium, sodium 5 mg
- store at 25°(77°F); excursions permitted between 15o-30oC (59o-86oF)
- Tamper Evident: Do not use if safetyseal under cap is broken or missing

Inactive ingredients

crosscarmellose Sodium, D&C Yellow# 10, dicalcium phosphate, FD&C Yellow #6, magnesium stearate, microcrystalline cellulose, polyvinyl alcohol, polyethylene glycol, sodium benzoate, talc, titanium dioxide

Questions or comments?

(866) 562-2756 Mon-Fri 8 AM to 4 PM EST

PACKAGE LABEL

PHARBEST

NDC 16103-378-08

Manufactured in the USA

*Compare to the active ingredients in Senokot-S®

SENNA-S

Sennosides 8.6mg &

Docusate Sodium 50mg

Natural Vegetable Laxative

Ingredient Plus Stool Softner

100 TABLETS